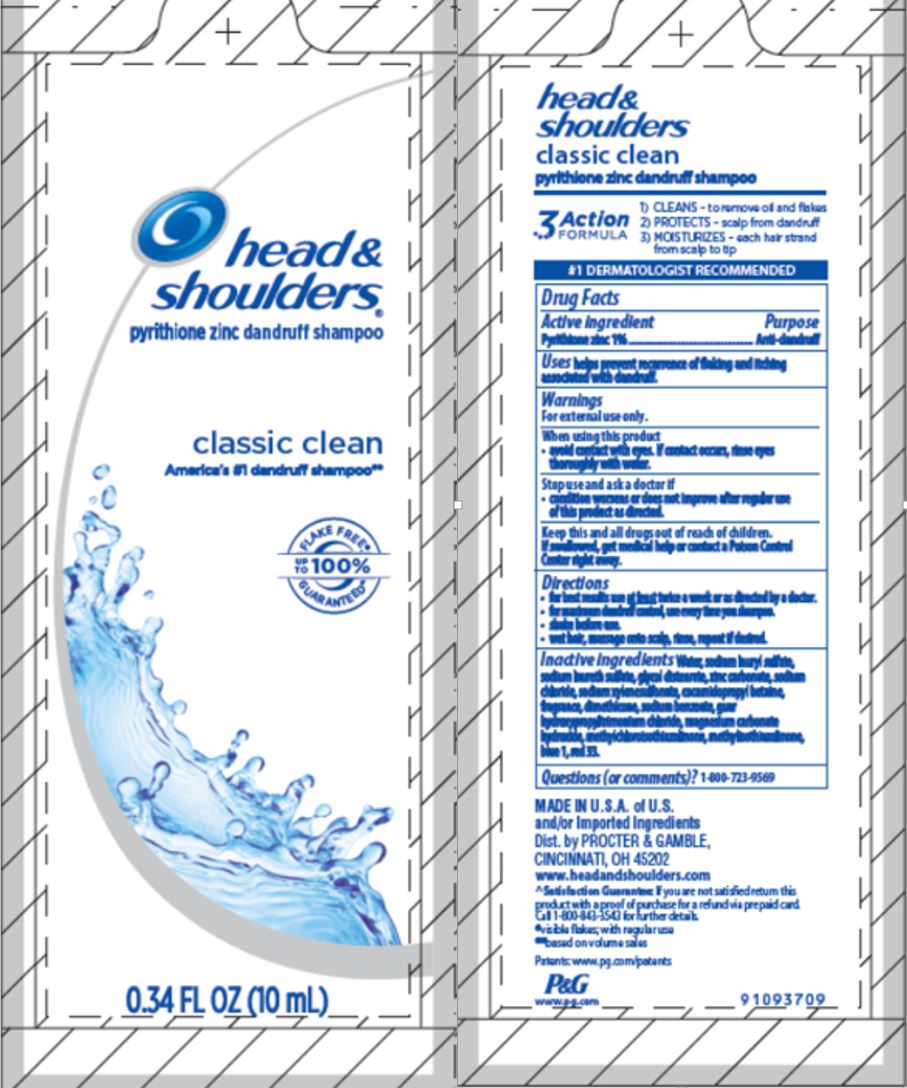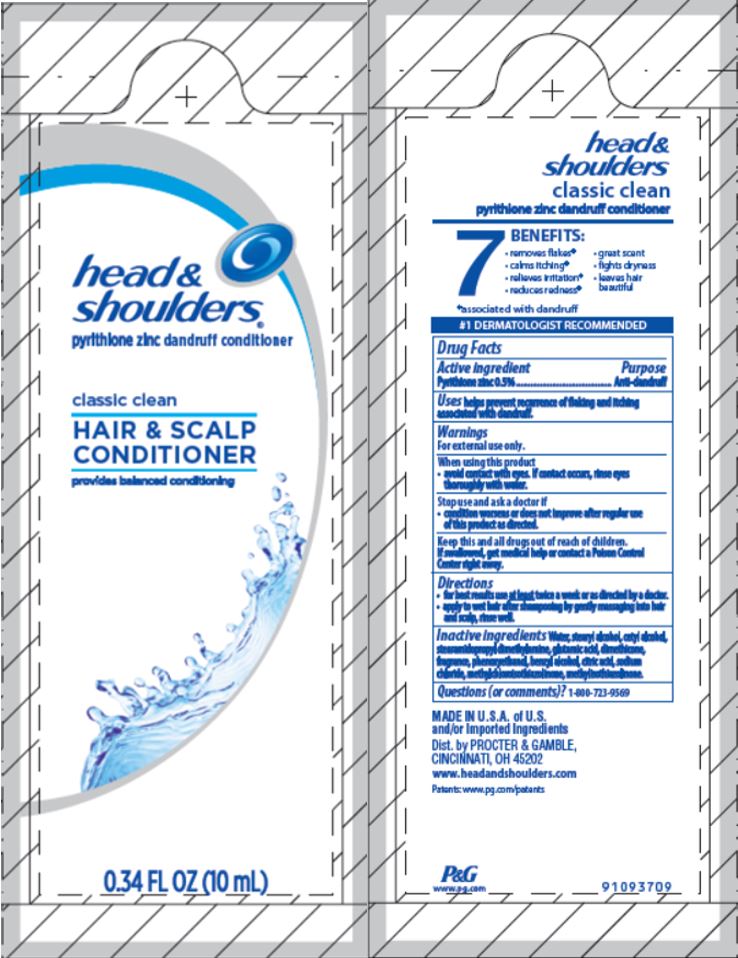 DRUG LABEL: Head and Shoulders Dual Sachets
NDC: 37000-106 | Form: KIT | Route: TOPICAL
Manufacturer: The Procter & Gamble Manufacturing Company
Category: otc | Type: HUMAN OTC DRUG LABEL
Date: 20190911

ACTIVE INGREDIENTS: PYRITHIONE ZINC 1 g/100 mL; PYRITHIONE ZINC 0.5 g/100 mL
INACTIVE INGREDIENTS: MAGNESIUM CARBONATE HYDROXIDE; METHYLCHLOROISOTHIAZOLINONE; METHYLISOTHIAZOLINONE; FD&C BLUE NO. 1; D&C RED NO. 33; WATER; SODIUM LAURYL SULFATE; SODIUM LAURETH-3 SULFATE; GLYCOL DISTEARATE; ZINC CARBONATE; SODIUM CHLORIDE; SODIUM XYLENESULFONATE; COCAMIDOPROPYL BETAINE; DIMETHICONE; SODIUM BENZOATE; STEARYL ALCOHOL; WATER; CETYL ALCOHOL; STEARAMIDOPROPYL DIMETHYLAMINE; GLUTAMIC ACID; PHENOXYETHANOL; BENZYL ALCOHOL; SODIUM CHLORIDE; METHYLISOTHIAZOLINONE; DIMETHICONE; CITRIC ACID MONOHYDRATE; METHYLCHLOROISOTHIAZOLINONE

Head and Shoulders® Dual Sachets
Classic Clean

head &
shoulders
classic clean
pyrithione zinc dandruff shampoo

Drug Facts

Active ingredient

Pyrithione zinc 1%

Purpose

Anti-dandruff

Uses

helps prevent recurrence of flaking and itching associated with dandruff.

Warnings

For external use only.

When using this product

- avoid contact with eyes. If contact occurs, rinse eyes thoroughly with water.

Stop use and ask a doctor if

- condition worsens or does not improve after regular use of this product as directed.

KEEP OUT OF REACH OF CHILDREN

Keep this and all drugs out of reach of children.

If swallowed, get medical help or contact a Poison Control Center right away.

Directions

- for best results use at least twice a week or as directed by a doctor.
- for maximum dandruff control, use every time you shampoo.
- shake before use.
- wet hair, massage onto scalp, rinse, repeat if desired.

Inactive ingredients

Water, sodium lauryl sulfate, sodium laureth sulfate, glycol distearate, zinc carbonate, sodium chloride, sodium xylenesulfonate, cocamidopropyl betaine, fragrance, dimethicone, sodium benzoate, guar hydroxypropyltrimonium chloride, magnesium carbonate hydroxide, methylchloroisothiazolinone, methylisothiazolinone, blue 1, red 33.

Questions (or comments)?

1-800-723-9569

head &
shoulders
classic clean
pyrithione zinc dandruff conditioner

Drug Facts

Active ingredient

Pyrithione zinc 0.5%

Purpose

Anti-dandruff

Uses

helps prevent recurrence of flaking and itching associated with dandruff.

Warnings

For external use only.

When using this product

- avoid contact with eyes. If contact occurs, rinse eyes thoroughly with water.

Stop use and ask a doctor if

- condition worsens or does not improve after regular use of this product as directed.

KEEP OUT OF REACH OF CHILDREN

Keep this and all drugs out of reach of children.

If swallowed, get medical help or contact a Poison Control Center right away.

Directions

- for best results use at least twice a week or as directed by a doctor.
- apply to wet hair after shampooing by gently massaging into hair and scalp, rinse well.

Inactive ingredients

Water, stearyl alcohol, cetyl alcohol, stearamidopropyl dimethylamine, glutamic acid, dimethicone, fragrance, phenoxyethanol, benzyl alcohol, citric acid, sodium chloride, methylchloroisothiazolinone, methylisothiazolinone.

Questions (or comments)?

1-800-723-9569

Dist. by PROCTER & GAMBLE,
CINCINNATI, OH 45202

PRINCIPAL DISPLAY PANEL - 10 mL Pouch Label - Shampoo

head &
shoulders ®

pyrithione zinc dandruff shampoo

classic clean

america's #1 dandruff shampoo**
FLAKE FREE,*
UP TO
100%
GURANTEED^

0.34 FL OZ (10 mL)

PRINCIPAL DISPLAY PANEL - 10 mL Pouch Label - Conditioner

head &
shoulders ®

pyrithione zinc dandruff conditioner

classic clean

HAIR & SCALP

CONDITIONER

provides balanced conditioning

0.34 FL OZ (10 mL)